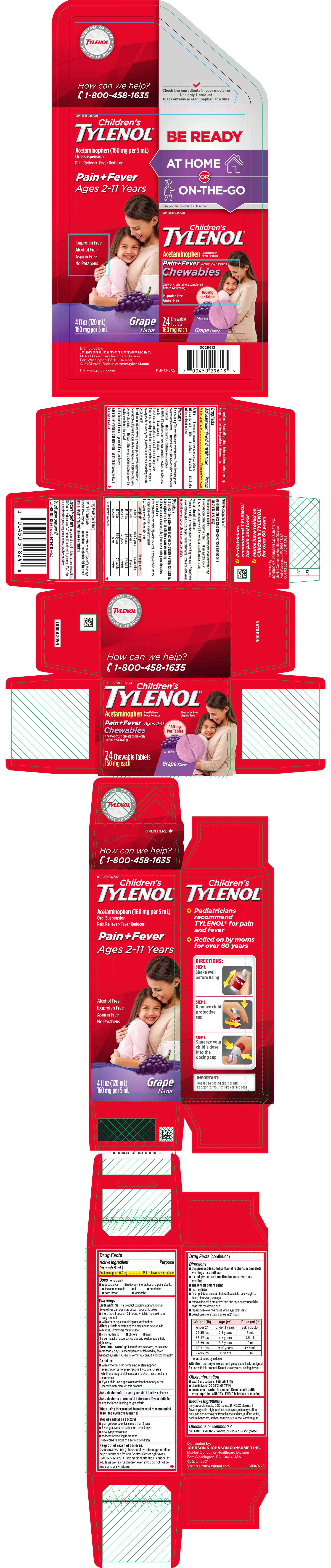 DRUG LABEL: Childrens Tylenol
NDC: 50580-460 | Form: KIT | Route: ORAL
Manufacturer: Kenvue Brands LLC
Category: otc | Type: HUMAN OTC DRUG LABEL
Date: 20241108

ACTIVE INGREDIENTS: ACETAMINOPHEN 160 mg/1 1; ACETAMINOPHEN 160 mg/5 mL
INACTIVE INGREDIENTS: SUCRALOSE; CELLULOSE ACETATE; CROSPOVIDONE; ANHYDROUS CITRIC ACID; D&C RED NO. 7; D&C RED NO. 30; ALUMINUM OXIDE; DEXTROSE, UNSPECIFIED FORM; FD&C BLUE NO. 1 ALUMINUM LAKE; MAGNESIUM STEARATE; POVIDONE, UNSPECIFIED; ANHYDROUS CITRIC ACID; D&C RED NO. 33; FD&C BLUE NO. 1; GLYCERIN; HIGH FRUCTOSE CORN SYRUP; MICROCRYSTALLINE CELLULOSE; CARBOXYMETHYLCELLULOSE SODIUM, UNSPECIFIED FORM; WATER; SODIUM BENZOATE; SORBITOL SOLUTION; SUCRALOSE; XANTHAN GUM

Children's Tylenol

Childrens Tylenol

Drug Facts

Active ingredient (in each chewable tablet)

Acetaminophen 160 mg

Purpose

Pain reliever/fever reducer

Uses

- temporarily relieves minor aches and pains due to:
  - the common cold
  - flu
  - headache
  - sore throat
  - toothache
- temporarily reduces fever

Warnings

Liver warning

This product contains acetaminophen. Severe liver damage may occur if your child takes

- more than 5 doses in 24 hours, which is the maximum daily amount
- with other drugs containing acetaminophen

Allergy alert: acetaminophen may cause severe skin reactions. Symptoms may include:

- skin reddening
- blisters
- rash

If a skin reaction occurs, stop use and seek medical help right away.

Sore throat warning: if sore throat is severe, persists for more than 2 days, is accompanied or followed by fever, headache, rash, nausea, or vomiting, consult a doctor promptly.

Do not use

- with any other drug containing acetaminophen (prescription or nonprescription). If you are not sure whether a drug contains acetaminophen, ask a doctor or pharmacist.
- if your child is allergic to acetaminophen or any of the inactive ingredients in this product

Ask a doctor before use if your child has liver disease

Ask a doctor or pharmacist before use if your child is taking the blood thinning drug warfarin

When using this product do not exceed recommended dose (see overdose warning)

Stop use and ask a doctor if

- pain gets worse or lasts more than 5 days
- fever gets worse or lasts more than 3 days
- new symptoms occur
- redness or swelling is present.

These could be signs of a serious condition.

Keep out of reach of children.

Overdose warning

In case of overdose, get medical help or contact a Poison Control Center right away. (1-800-222-1222) Quick medical attention is critical for adults as well as for children even if you do not notice any signs or symptoms.

Directions

- this product does not contain directions or complete warnings for adult use.
- do not give more than directed (see overdose warning)
- chew or crush tablets completely before swallowing; do not swallow tablets whole
- find right dose on chart below. If possible, use weight to dose; otherwise, use age.
- repeat dose every 4 hours while symptoms last
- do not give more than 5 times in 24 hours

Weight (lb) | Age (yr) | Dose (tablets) [or as directed by a doctor]
under 24 | under 2 years | ask a doctor
24-35 lbs | 2-3 years | 1 tablet
36-47 lbs | 4-5 years | 1½ tablets
48-59 lbs | 6-8 years | 2 tablets
60-71 lbs | 9-10 years | 2½ tablets
72-95 lbs | 11 years | 3 tablets

Other information

- store between 20-25°C (68-77°F). Avoid high humidity. Protect from light.
- do not use if neck band or foil inner seal imprinted with "TYLENOL" is broken or missing

Inactive ingredients

anhydrous citric acid, cellulose acetate, crospovidone, D&C red no. 7 calcium lake, D&C red no. 30 aluminum lake, dextrose, FD&C blue no. 1 aluminum lake, flavor, magnesium stearate, povidone, sucralose

Questions or comments?

call 1-800-458-1635 (toll-free) or 215-273-8755 (collect)

Childrens Tylenol

Drug Facts

Active ingredient (in each 5 mL)

Acetaminophen 160 mg

Purpose

Pain reliever/fever reducer

Uses

temporarily:

- reduces fever
- relieves minor aches and pains due to:
  - the common cold
  - flu
  - headache
  - sore throat
  - toothache

Warnings

Liver warning

This product contains acetaminophen. Severe liver damage may occur if your child takes

- more than 5 doses in 24 hours, which is the maximum daily amount
- with other drugs containing acetaminophen

Allergy alert: acetaminophen may cause severe skin reactions. Symptoms may include:

- skin reddening
- blisters
- rash

If a skin reaction occurs, stop use and seek medical help right away.

Sore throat warning: if sore throat is severe, persists for more than 2 days, is accompanied or followed by fever, headache, rash, nausea, or vomiting, consult a doctor promptly.

Do not use

- with any other drug containing acetaminophen (prescription or nonprescription). If you are not sure whether a drug contains acetaminophen, ask a doctor or pharmacist.
- if your child is allergic to acetaminophen or any of the inactive ingredients in this product

Ask a doctor before use if your child has liver disease

Ask a doctor or pharmacist before use if your child is taking the blood thinning drug warfarin

When using this product do not exceed recommended dose (see overdose warning)

Stop use and ask a doctor if

- pain gets worse or lasts more than 5 days
- fever gets worse or lasts more than 3 days
- new symptoms occur
- redness or swelling is present

These could be signs of a serious condition.

Keep out of reach of children.

Overdose warning

In case of overdose, get medical help or contact a Poison Control Center right away. (1-800-222-1222) Quick medical attention is critical for adults as well as for children even if you do not notice any signs or symptoms.

Directions

- this product does not contain directions or complete warnings for adult use.
- do not give more than directed (see overdose warning)
- shake well before using
- mL = milliliter
- find right dose on chart below. If possible, use weight to dose; otherwise, use age.
- remove the child protective cap and squeeze your child's dose into the dosing cup
- repeat dose every 4 hours while symptoms last
- do not give more than 5 times in 24 hours

Weight (lb) | Age (yr) | Dose (mL) [or as directed by a doctor]
under 24 | under 2 years | ask a doctor
24-35 lbs | 2-3 years | 5 mL
36-47 lbs | 4-5 years | 7.5 mL
48-59 lbs | 6-8 years | 10 mL
60-71 lbs | 9-10 years | 12.5 mL
72-95 lbs | 11 years | 15 mL

Attention: use only enclosed dosing cup specifically designed for use with this product. Do not use any other dosing device.

Other information

- each 5 mL contains: sodium 2 mg
- store between 20-25°C (68-77°F)
- do not use if carton is opened. Do not use if bottle wrap imprinted with “TYLENOL” is broken or missing

Inactive ingredients

anhydrous citric acid, D&C red no. 33, FD&C blue no. 1, flavors, glycerin, high fructose corn syrup, microcrystalline cellulose and carboxymethylcellulose sodium, purified water, sodium benzoate, sorbitol solution, sucralose, xanthan gum

Questions or comments?

call 1-800-458-1635 (toll-free) or 215-273-8755 (collect)

PRINCIPAL DISPLAY PANEL

NDC 50580-460-01

Children's
TYLENOL ®

Acetaminophen (160 mg per 5 mL)
Oral Suspension

Pain Reliever-Fever Reducer

Pain+Fever
Ages 2-11 Years

Ibuprofen Free
Alcohol Free
Aspirin Free

No Parabens

4 fl oz (120 mL)
160 mg per 5 mL
Grape
Flavor

BE READY
AT HOME
OR
ON-THE-GO

Use products only as directed

NDC 50580-460-01

Children's
TYLENOL ®

Acetaminophen
Pain Reliever
Fever Reducer

Pain+Fever
Ages 2-11
Chewables

Chew or crush tablets completely
before swallowing

Ibuprofen Free

Aspirin Free

160 mg
Per Tablet

24
Chewable
Tablets
Actual Size
160 mg each
Grape Flavor